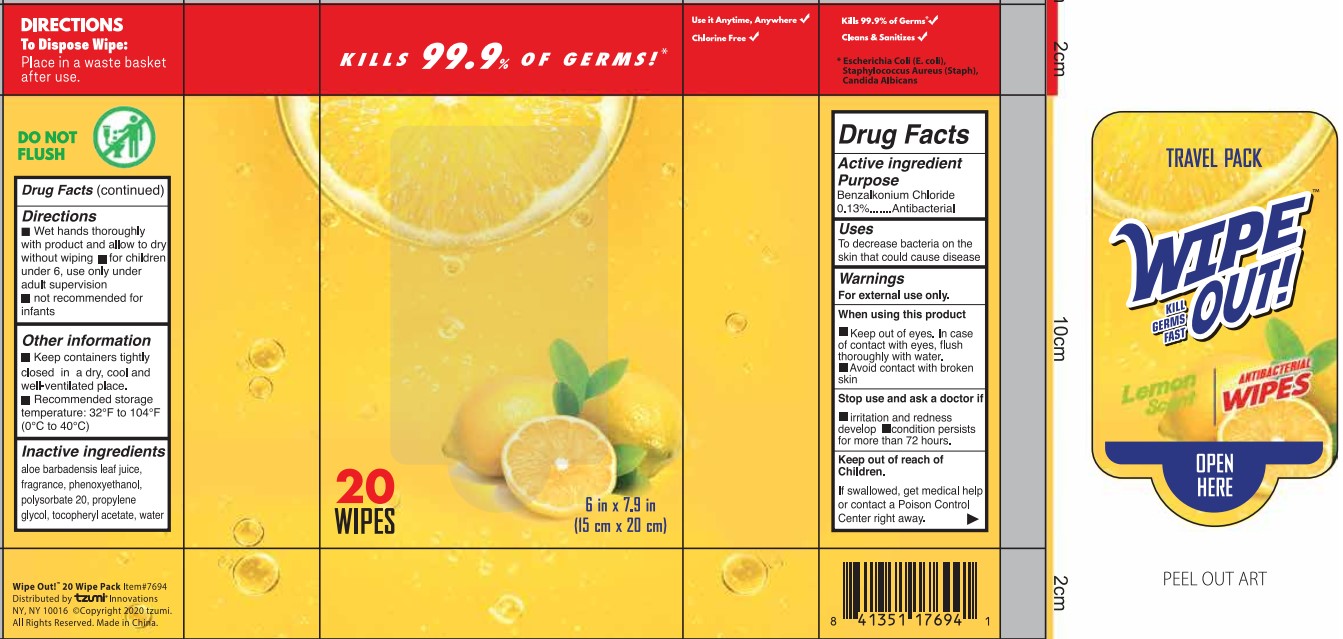 DRUG LABEL: Antibacterial Wipes
NDC: 42003-012 | Form: CLOTH
Manufacturer: Zhejiang Jiayan Daily Commodity Co., Ltd.
Category: otc | Type: HUMAN OTC DRUG LABEL
Date: 20200811

ACTIVE INGREDIENTS: BENZALKONIUM CHLORIDE 0.13 g/100 g
INACTIVE INGREDIENTS: PHENOXYETHANOL 0.3 g/100 g; .ALPHA.-TOCOPHEROL ACETATE 0.2 g/100 g; ALOE 0.2 g/100 g; FRAGRANCE LAVENDER & CHIA F-153480 0.03 g/100 g; WATER 97.94 g/100 g; POLYSORBATE 20 0.2 g/100 g; PROPYLENE GLYCOL 1 g/100 g

Active Ingredient(s)

Benzalkonium Chloride 0.13% w/w. Purpose: Antiseptic

Purpose

Antiseptic, Hand Sanitizer

Use

To decreases bacteria and germs on the skin that could cause disease.

Warnings

For external use only.

Do not use

- in children less than 2 months of age
- on open skin wounds

When using this product keep out of eyes, ears, and mouth. In case of contact with eyes, rinse eyes thoroughly with water.
Stop use and ask a doctor if irritation or rash occurs. These may be signs of a serious condition.
Keep out of reach of children. If swallowed, get medical help or contact a Poison Control Center right away.

Stop use and ask a doctor if

- irritation and redness develop.
- condition persists for more than 72 hours.

Keep out of reach of children. If swallowed, get medical help or contact a Poison Control Center right away.

Directions

- Wet hands thoroughly with product and allow to dry without wiping.
- For children under 6, use only under adult supervision.
- Not recommended for infants.

Other information

- Keep containers tightly closed in a dry, cool and well-ventilated place.
- Recommended storage temperature: 32F to 104F(0C to 4C).

Inactive ingredients

aloe barbadensis leaf juice, fragrance, phenoxyethanol, polysorbate 20, propylene glycol, tocopheryl acetate, water.

Package Label - Principal Display Panel

20 Wipes in 1 BAG NDC: 42003-012-03